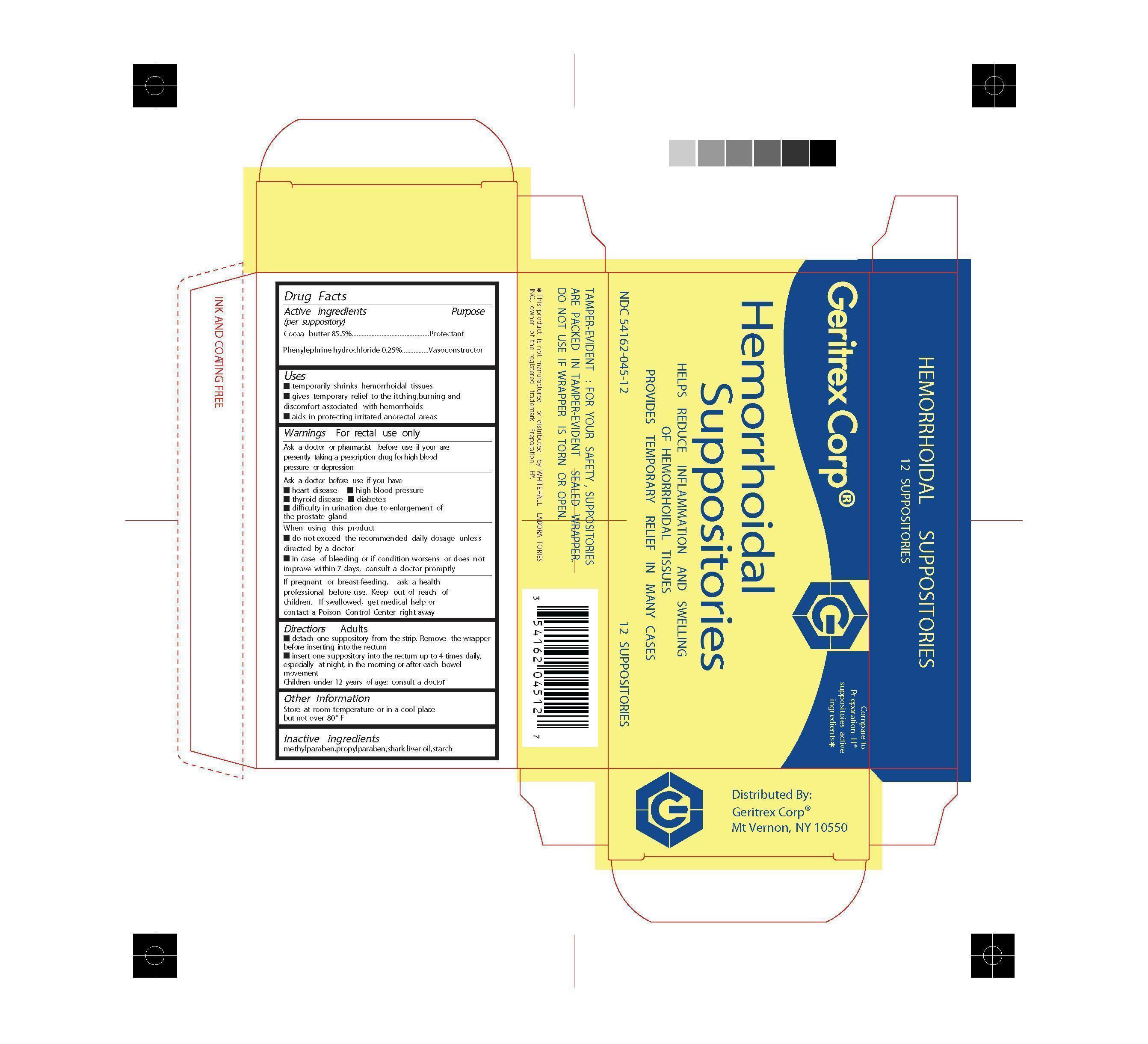 DRUG LABEL: HEMORRHOIDAL
NDC: 54162-045 | Form: SUPPOSITORY
Manufacturer: Geritrex Corp.
Category: otc | Type: HUMAN OTC DRUG LABEL
Date: 20141016

ACTIVE INGREDIENTS: PHENYLEPHRINE HYDROCHLORIDE 0.25 g/100 g; COCOA BUTTER 85.5 g/100 g
INACTIVE INGREDIENTS: METHYLPARABEN; PROPYLPARABEN; SHARK LIVER OIL; STARCH, CORN

Hemorrhoidal Suppositories

Drug Facts

Active Ingredients Purpose
(per suppository)
Cocoa butter 85.5%...............................................Protectant
Phenylephrine hydrochloride 0.25%................Vasoconstructor

Uses

temporarily shrinks hemorrhoidal tissues
gives temporary relief to the itching,burning and
discomfort associated with hemorrhoids
aids in protecting irritated anorectal areas

Directions

detach one suppository from the strip. Remove the wrapper
before inserting into the rectum
insert one suppository into the rectum up to 4 times daily,
especially at night, in the morning or after each bowel
movement

DOSAGE AND ADMINISTRATION

Children under 12 years of age: consult a doctor

WARNINGS

For rectal use only
Ask a doctor or pharmacist before use if your are
presently taking a prescription drug for high blood
pressure or depression
Ask a doctor before use if you have
heart disease high blood pressure
thyroid disease diabetes diffculty urination due to enlargement of
the prostate gland
When using this product
do not exceed the recommended daily dosage unless
directed by a doctor
in case of bleeding or if condition worsens or does not
improve within 7 days, consult a doctor promptly
If pregnant or breast-feeding, ask a health
professional before use. Keep out of reach of
children. If swallowed, get medical help or
contact a Poison Control Center right away

INACTIVE INGREDIENT

methylparaben,propylparaben,shark liver oil,starch

STORAGE

Store at room temperature or in a cool place
but not over 80° F

KEEP OUT OF REACH OF CHILDREN

If swallowed, get medical help or
contact a Poison Control Center right away